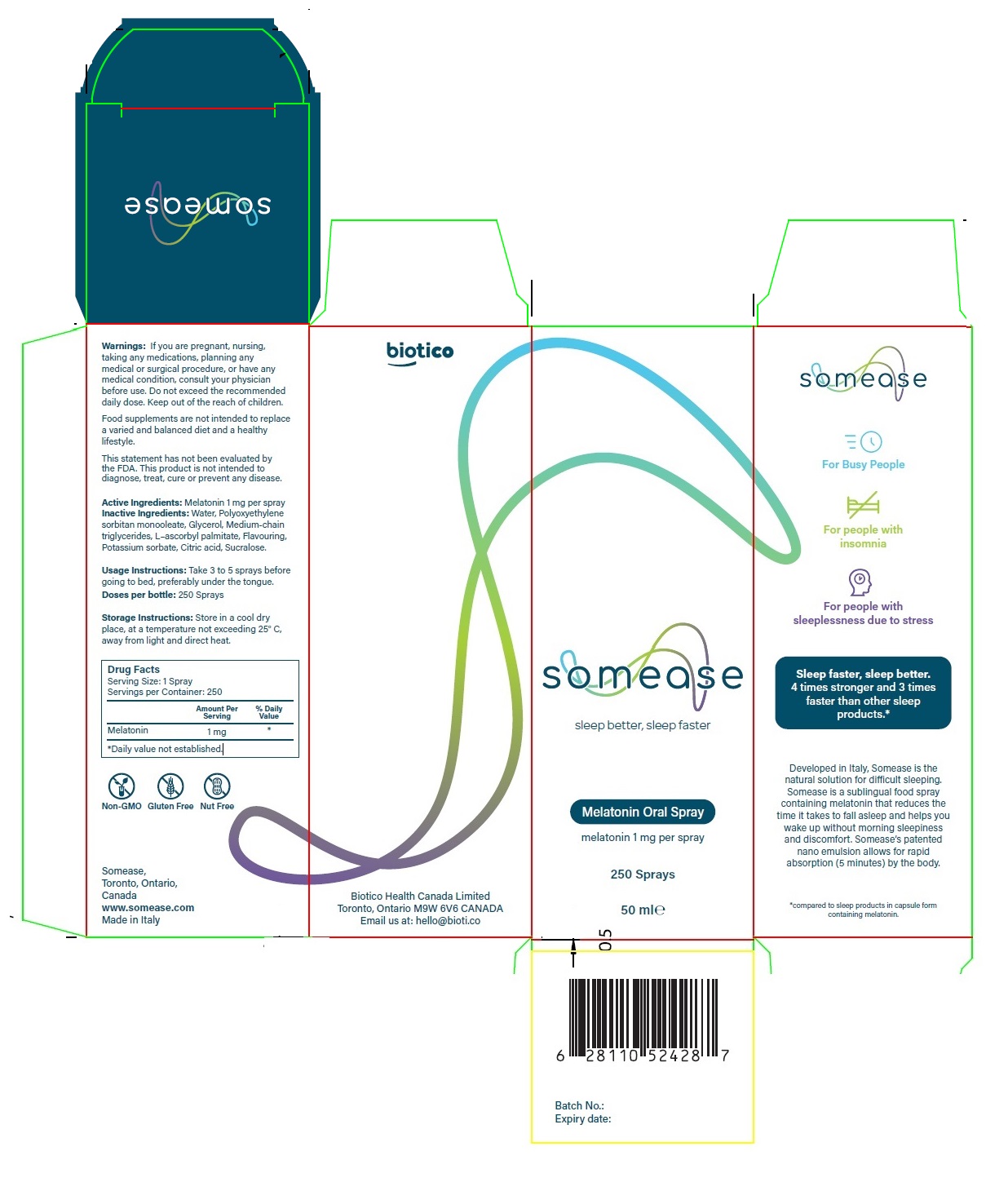 DRUG LABEL: somease
NDC: 71902-100 | Form: SPRAY, METERED
Manufacturer: Biotico Health Canada Limited
Category: homeopathic | Type: HUMAN OTC DRUG LABEL
Date: 20171201

ACTIVE INGREDIENTS: MELATONIN 1 mg/0.2 mL
INACTIVE INGREDIENTS: WATER; PEG-6 SORBITAN OLEATE; GLYCERIN; MEDIUM-CHAIN TRIGLYCERIDES; ASCORBYL PALMITATE; POTASSIUM SORBATE; CITRIC ACID MONOHYDRATE; SUCRALOSE

somease

Active Ingredients:

Melatonin 1 mg per spray

PURPOSE

Relieve symptoms associated with sleeplessness

INDICATIONS AND USAGE

Solution for difficult sleeping.

For people with sleeplessness due to stress or for people with insomnia.

Warnings:

If you are pregnant, nursing, taking any medications, planning any medical or surgical procedure, or have any medical condition, consult your physician before use. Do not exceed the recommended daily dose.

Keep out of the reach of children.

Usage Instructions:

Take 3 to 5 sprays before going to bed, preferably under the tongue.

Doses per bottle: 250 Sprays

Inactive Ingredients:

Water, Polyoxyethylene sorbitan monooleate, Glycerol, Medium-chain triglycerides, L–ascorbyl palmitate, Flavouring, Potassium sorbate, Citric acid, Sucralose.

Storage Instructions:

Store in a cool dry place, at a temperature not exceeding 25° C, away from light and direct heat.

Melatonin Oral Spray

For Busy People

For people with insomnia

For people with sleeplessness due to stress

Sleep faster, sleep better. 4 times stronger and 3 times faster than other sleep products.*

Developed in Italy, Somease is the natural solution for difficult sleeping. Somease is a sublingual food spray containing melatonin that reduces the time it takes to fall asleep and helps you wake up without morning sleepiness and discomfort. Somease’s patented nano emulsion allows for rapid absorption (5 minutes) by the body.

*compared to sleep products in capsule form containing melatonin.

Non-GMO

Gluten Free

Nut Free

Somease,Toronto, Ontario, Canada

www.somease.com

Made in Italy

Biotico Health Canada Limited Toronto, Ontario M9W 6V6 CANADA

Email us at: hello@bioti.co